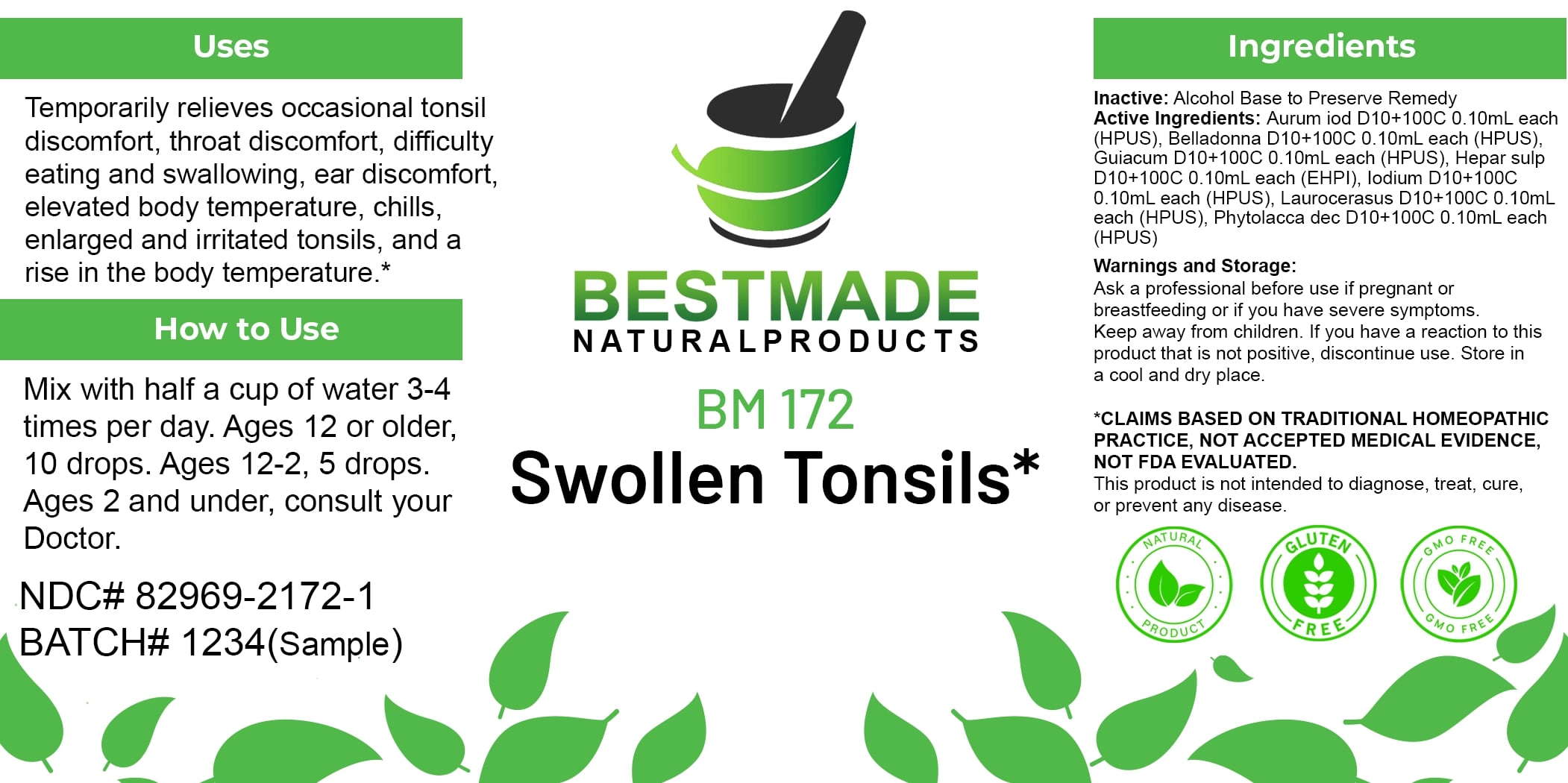 DRUG LABEL: Bestmade Natural Products BM172
NDC: 82969-2172 | Form: LIQUID
Manufacturer: Bestmade Natural Products
Category: homeopathic | Type: HUMAN OTC DRUG LABEL
Date: 20250219

ACTIVE INGREDIENTS: PRUNUS LAUROCERASUS LEAF 30 [hp_C]/30 [hp_C]; ATROPA BELLADONNA 30 [hp_C]/30 [hp_C]; IODINE 30 [hp_C]/30 [hp_C]; CALCIUM SULFIDE 30 [hp_C]/30 [hp_C]; GUAIACUM OFFICINALE RESIN 30 [hp_C]/30 [hp_C]; GOLD MONOIODIDE 30 [hp_C]/30 [hp_C]; PHYTOLACCA AMERICANA ROOT 30 [hp_C]/30 [hp_C]
INACTIVE INGREDIENTS: ALCOHOL 30 [hp_C]/30 [hp_C]

BM172

DOSAGE AND ADMINISTRATION

How to Use

Mix with half a cup of water 3-4 times per day. Ages 12 or older, 10 drops. Ages 12-2, 5 drops. Ages 2 and under, consult your Doctor.

INACTIVE INGREDIENT

Ingredients

Inactive: Alcohol Base to Preserve Remedy

ACTIVE INGREDIENT

Active Ingredients: Aurum iod D10+100C 0.10ml each (HPUS), Belladonna D10+100C 0.10ml each (HPUS), Guaiacum D10+100C 0.10ml each (HPUS), Hepar sulph D10+100C 0.10ml each (EHP), Iodium D10+100C 0.10ml each (HPUS), Laurocerasus D10+100C 0.10ml each (HPUS), Phytolacca dec D10+100C 0.10ml each (HPUS)

Uses

Temporarily relieves occasional tonsil discomfort, throat discomfort, difficulty eating and swallowing, ear discomfort, elevated body temperature, chills, enlarged and irritated tonsils, and a rise in the body temperature.*

*CLAIMS BASED ON TRADITIONAL HOMEOPATHIC PRACTICE. NOT ACCEPTED MEDICAL EVIDENCE. NOT FDA EVALUATED.

This product is not intended to diagnose, treat, cure, or prevent any disease.

Uses

Temporarily relieves occasional tonsil discomfort, throat discomfort, difficulty eating and swallowing, ear discomfort, elevated body temperature, chills, enlarged and irritated tonsils, and a rise in the body temperature.*

*CLAIMS BASED ON TRADITIONAL HOMEOPATHIC PRACTICE. NOT ACCEPTED MEDICAL EVIDENCE. NOT FDA EVALUATED.

This product is not intended to diagnose, treat, cure, or prevent any disease.

KEEP OUT OF REACH OF CHILDREN

Warnings and Storage:

Ask a professional before use if pregnant or breastfeeding or if you have severe symptoms. Keep away from children. If you have a reaction to this product that is not positive, discontinue use. Store in a cool and dry place.

Warnings and Storage:

Ask a professional before use if pregnant or breastfeeding or if you have severe symptoms. Keep away from children. If you have a reaction to this product that is not positive, discontinue use. Store in a cool and dry place.

*CLAIMS BASED ON TRADITIONAL HOMEOPATHIC PRACTICE. NOT ACCEPTED MEDICAL EVIDENCE. NOT FDA EVALUATED.

This product is not intended to diagnose, treat, cure, or prevent any disease.

Entire package label